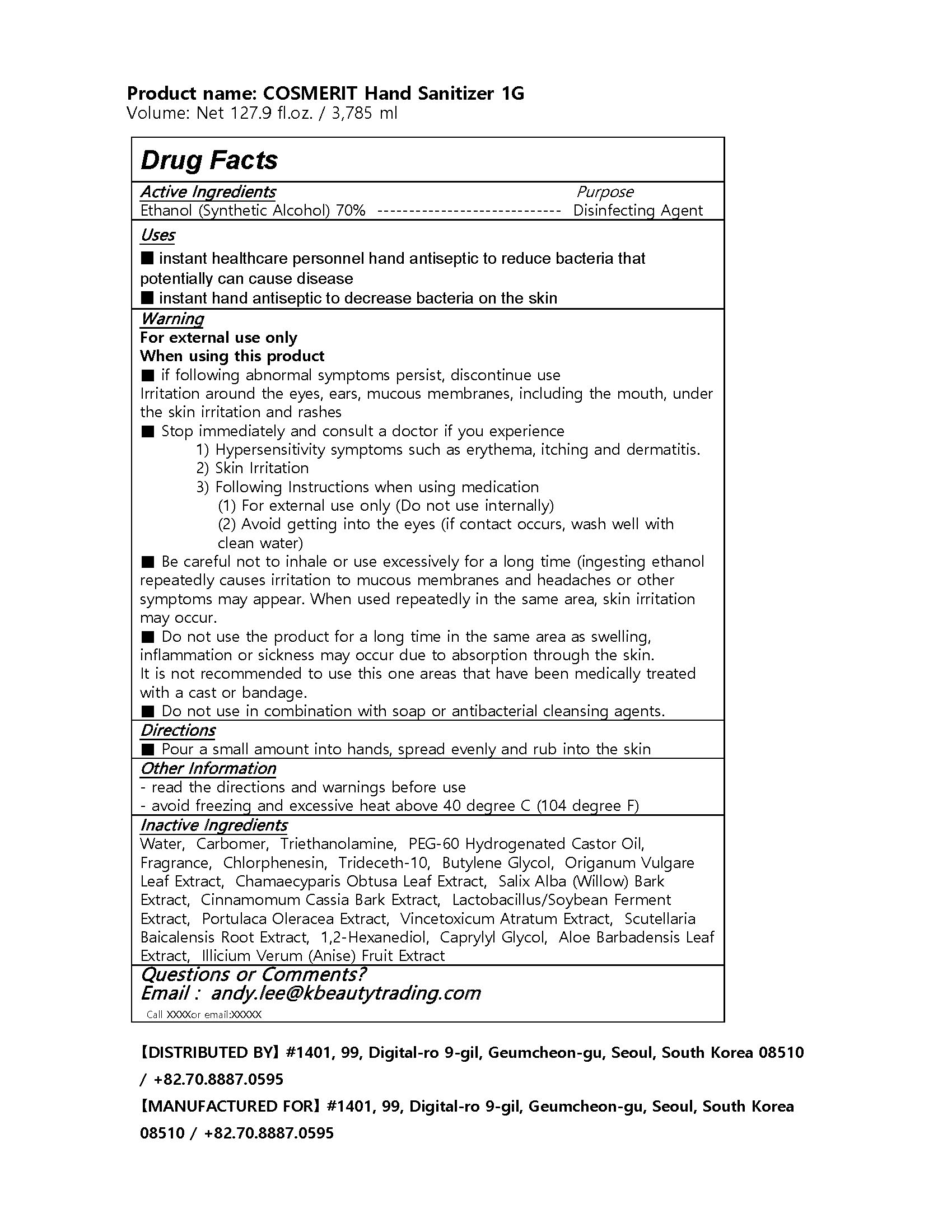 DRUG LABEL: COSMERIT Hand Sanitizer 1G
NDC: 77049-0003 | Form: GEL
Manufacturer: Interkos Co.,Ltd.
Category: otc | Type: HUMAN OTC DRUG LABEL
Date: 20200704

ACTIVE INGREDIENTS: ALCOHOL 70 mL/100 mL
INACTIVE INGREDIENTS: PEG-60 HYDROGENATED CASTOR OIL; WATER; CARBOMER 934; TROLAMINE; CHLORPHENESIN; BUTYLENE GLYCOL

Drug Facts

ACTIVE INGREDIENT

Alcohol

INACTIVE INGREDIENT

Water, Carbomer, Triethanolamine, PEG-60 Hydrogenated Castor Oil, Fragrance, Chlorphenesin, Trideceth-10, Butylene Glycol, Origanum Vulgare Leaf Extract, Chamaecyparis Obtusa Leaf Extract, Salix Alba (Willow) Bark Extract, Cinnamomum Cassia Bark Extract, Lactobacillus/Soybean Ferment Extract, Portulaca Oleracea Extract, Vincetoxicum Atratum Extract, Scutellaria Baicalensis Root Extract, 1,2-Hexanediol, Caprylyl Glycol, Aloe Barbadensis Leaf Extract, Illicium Verum (Anise) Fruit Extract

PURPOSE

■ instant healthcare personnel hand antiseptic to reduce bacteria that potentially can cause disease

■ instant hand antiseptic to decrease bacteria on the skin

KEEP OUT OF REACH OF THE CHILDREN

INDICATIONS AND USAGE

Pump an appropriate amount on to the hands and rub together until dry

WARNINGS

1. Do not use this product on the following parts of body. Around eyes and ears, oral cavity, large area of the
parts of body, or wounded skins (It may cause irritations)
2. Stop using at once in case of the following symptoms, and seek medical advice. 1) When eczema, red spots,
itchiness, edema, and allergic reactions occur. 2)When skin irritations happen.
3. Other user reminders 1) For external use only(No oral intake). 2) Avoid contact with eyes, and in case contact
occurs, rinse it thoroughly with clean water and consult a doctor or pharmacist. 3) When you use it on a large skin
area or use it long-termly, please be aware that vapor is not absorbed. (If Ethanol vapor is largely and repeatedly
inhaled and absorbed, it may cause irritation to mucous membrane and headache might occur.) 4)When the product
is used on the same part of skin repeatedly, the skin may become rough due to skimming. 5) Do not use with sealed
gauze bandage, Gibbs bandage or pack, as irritations may occur. 6) Do not use this product while anus and vagina
steaming as irritations or chemical burns may occur. 7) Do not use for purposes other than specified.

DOSAGE AND ADMINISTRATION

external use only